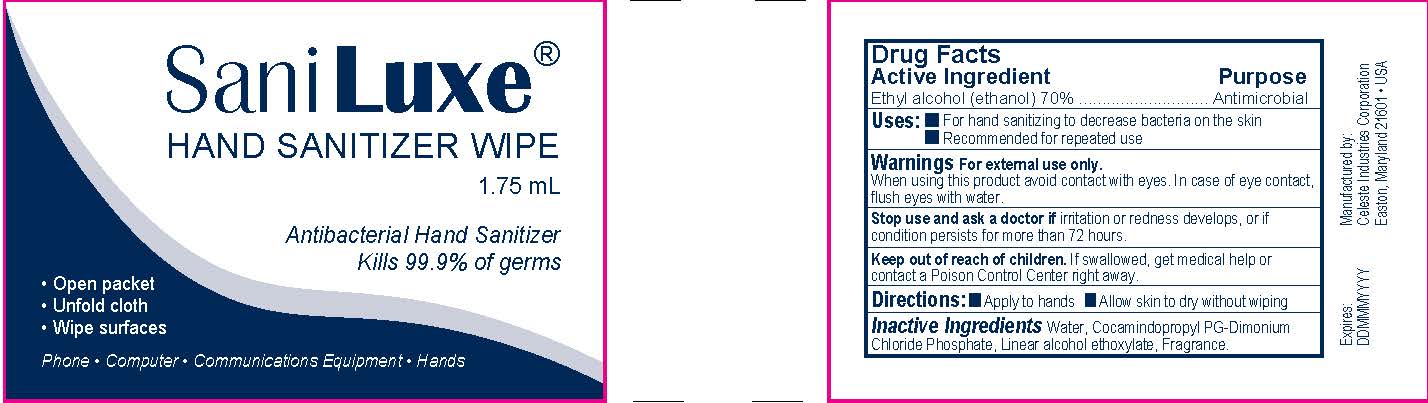 DRUG LABEL: Sani Luxe
NDC: 71489-009 | Form: CLOTH
Manufacturer: Celeste Industries Corporation
Category: otc | Type: HUMAN OTC DRUG LABEL
Date: 20240708

ACTIVE INGREDIENTS: ALCOHOL 0.7 mL/1 mL
INACTIVE INGREDIENTS: COCAMIDOPROPYL PG-DIMONIUM CHLORIDE PHOSPHATE; WATER; C9-11 PARETH-6

Sani Luxe

Drug Facts

Active Ingredient

Ethyl alcohol (ethanol) 70%

Purpose

Antimicrobial

Uses

- For hand sanitizing to decrease bacteria on the skin
- Recommended for repeated use

Warning

For external use only.

When using this product avoid contact with eyes. In case of eye contact,
flush eyes with water.

Stop use and ask a doctor if irritation or redness develops, or if
condition persists for more than 72 hours.

Keep out of reach of children. If swallowed, get medical help or
contact a Poison Control Center right away.

Directions

- Apply to hands
- Allow skin to dry without wiping

Inactive Ingredients

Water, Cocamindopropyl PG-Dimonium, Chloride Phosphate, Linear alcohol ethoxylate, Fragrance.

Expires:
DDMMMYYYY

Manufactured by:
Celeste Industries Corporation
Easton, Maryland 21601 • USA